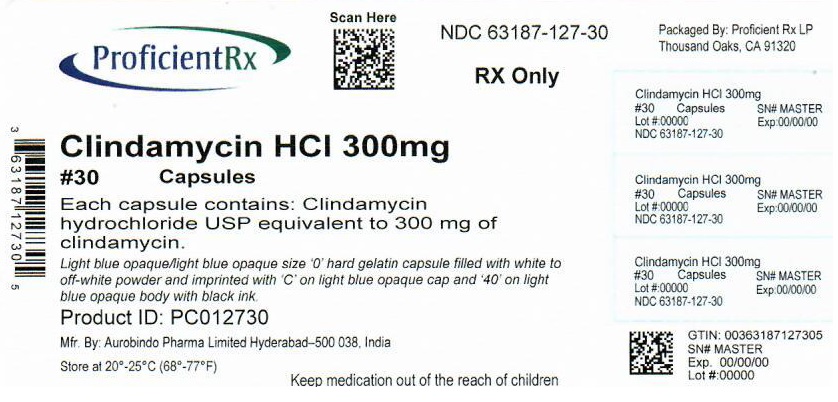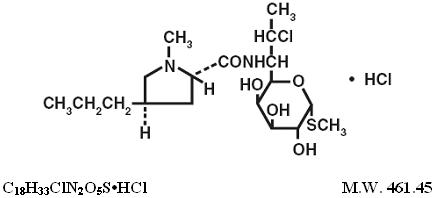 DRUG LABEL: Clindamycin Hydrochloride
NDC: 63187-127 | Form: CAPSULE
Manufacturer: Proficient Rx LP
Category: prescription | Type: HUMAN PRESCRIPTION DRUG LABEL
Date: 20220401

ACTIVE INGREDIENTS: CLINDAMYCIN HYDROCHLORIDE 300 mg/1 1
INACTIVE INGREDIENTS: LACTOSE MONOHYDRATE; STARCH, CORN; TALC; MAGNESIUM STEARATE; FD&C BLUE NO. 1; TITANIUM DIOXIDE; GELATIN, UNSPECIFIED; SODIUM LAURYL SULFATE; FERROSOFERRIC OXIDE; SHELLAC

Clindamycin Hydrochloride Capsules, USP

To reduce the development of drug-resistant bacteria and maintain the effectiveness of clindamycin hydrochloride and other antibacterial drugs, clindamycin hydrochloride should be used only to treat or prevent infections that are proven or strongly suspected to be caused by bacteria.

WARNING

Clostridium difficile associated diarrhea (CDAD) has been reported with use of nearly all antibacterial agents, including clindamycin hydrochloride and may range in severity from mild diarrhea to fatal colitis. Treatment with antibacterial agents alters the normal flora of the colon, leading to overgrowth of C. difficile.
Because clindamycin hydrochloride therapy has been asso‑ciated with severe colitis which may end fatally, it should be reserved for serious infec‑tions where less toxic antimicrobial agents are inappropriate, as described in the INDICA‑TIONS AND USAGE section. It should not be used in patients with nonbacterial infections such as most upper respiratory tract infections.
C. difficile produces toxins A and B, which contribute to the development of CDAD. Hypertoxin producing strains of C. difficile cause increased morbidity and mortality, as these infections can be refractory to antimicrobial therapy and may require colectomy. CDAD must be considered in all patients who present with diarrhea following antibiotic use. Careful medical history is necessary since CDAD has been reported to occur over two months after the administration of antibacterial agents.
If CDAD is suspected or confirmed, ongoing antibiotic use not directed against C. difficile may need to be discontinued. Appropriate fluid and electrolyte management, protein supplementation, antibiotic treatment of C. difficile, and surgical evaluation should be instituted as clinically indicated.

DESCRIPTION

Clindamycin hydrochloride is the hydrated hydrochlo‑ride salt of clindamycin. Clindamycin is a semisynthetic antibiotic produced by a 7(S)-chloro-substitution of the 7(R)-hydroxyl group of the parent compound lincomycin.
The chemical name for clindamycin hydrochloride is Methyl 7-chloro-6,7,8-trideoxy-6-(1-methyl-trans-4-propyl-L-2-pyrrolidinecarboxamido)-1-thio-L-threo-α-D-galacto-octopyranoside monohydrochloride.
The structural formula is represented below:

Clindamycin hydrochloride capsules, USP contain clindamycin hydro‑chloride USP equivalent to 150 mg or 300 mg of clindamycin. Each capsule also contains the following inactive ingredients: lactose monohydrate, corn starch, talc, and magnesium stearate. The empty hard gelatin capsule shell consists of FD&C Blue #1, titanium dioxide, gelatin, and sodium lauryl sulphate. In addition 150 mg also contains yellow iron oxide. The capsules are printed with edible ink containing black iron oxide and shellac.

CLINICAL PHARMACOLOGY

Human Pharmacology
Absorption
Serum level studies with a 150 mg oral dose of clindamycin hydrochloride in 24 normal adult volunteers showed that clindamycin was rapidly absorbed after oral administration. An average peak serum level of 2.5 mcg/mL was reached in 45 minutes; serum levels averaged 1.51 mcg/mL at 3 hours and 0.7 mcg/mL at 6 hours. Absorption of an oral dose is virtually complete (90%), and the concomitant admin‑istration of food does not appreciably modify the serum concentrations; serum levels have been uniform and predictable from person to person and dose to dose. Serum level studies following multiple doses of clindamycin hydrochloride for up to 14 days show no evidence of accumulation or altered metabolism of drug. Doses of up to 2 grams of clindamycin per day for 14 days have been well tolerated by healthy volunteers, except that the incidence of gastrointestinal side effects is greater with the higher doses.
Distribution
Concentrations of clindamycin in the serum increased linearly with increased dose. Serum levels exceed the MIC (minimum inhibitory concentration) for most indi‑cated organisms for at least six hours following adminis‑tration of the usually recommended doses. Clindamycin is widely distributed in body fluids and tissues (including bones). No significant levels of clindamycin are attained in the cerebrospinal fluid, even in the presence of inflamed meninges.
Excretion
The average biological half-life is 2.4 hours. Approximately 10% of the bioactivity is excreted in the urine and 3.6% in the feces; the remainder is excreted as bioinactive metabolites.
Special Populations
Renal Impairment
Serum half-life of clindamycin is increased slightly in patients with markedly reduced renal function. Hemodialysis and peritoneal dialysis are not effective in removing clindamycin from the serum.
Use in Elderly
Pharmacokinetic studies in elderly volunteers (61 to 79 years) and younger adults (18 to 39 years) indicate that age alone does not alter clindamycin pharmacokinetics (clearance, elimination half-life, volume of distribution, and area under the serum concentration-time curve) after IV administration of clindamycin phosphate. After oral administration of clindamycin hydrochloride, elimi‑nation half-life is increased to approximately 4 hours (range 3.4 to 5.1 h) in the elderly compared to 3.2 hours (range 2.1 to 4.2 h) in younger adults. The extent of absorption, however, is not different between age groups and no dosage alteration is necessary for the elderly with normal hepatic function and normal (age-adjusted) renal function.
Microbiology
Clindamycin inhibits bacterial protein synthesis by binding to the 50S subunit of the ribosome. It has activity against Gram-positive aerobes and anaer‑obes as well as some Gram-negative anaerobes. Clindamycin is bacteriostatic. Cross-resistance between clindamycin and lincomycin is complete. Antagonism in vitro has been demonstrated between clindamycin and erythromycin. Clindamycin inducible resistance has been identified in macrolide-resistant staphylococci and beta-hemolytic streptococci. Macrolide-resistant isolates of these organisms should be screened for clindamycin inducible resistance using the D-zone test.
Clindamycin has been shown to be active against most of the isolates of the following microorganisms, both in vitro and in clinical infections, as described in the INDICATIONS AND USAGE section.
Gram-positive aerobes
Staphylococcus aureus (methicillin-susceptible strains)
Streptococcus pneumoniae (penicillin-susceptible strains)
Streptococcus pyogenes
Anaerobes
Prevotella melaninogenica
Fusobacterium necrophorum
Fusobacterium nucleatum
Peptostreptococcus anaerobius
Clostridium perfringens
At least 90% of the microorganisms listed below exhibit in vitro minimum inhibitory concentrations (MICs) less than or equal to the clindamycin susceptible MIC breakpoint for organisms of a similar type to those shown in Table 1. However, the efficacy of clindamycin in treating clinical infections due to these microorganisms has not been established in adequate and well-controlled clinical trials.
Gram-positive aerobes
Staphylococcus epidermidis (methicillin-susceptible strains)
Streptococcus agalactiae
Streptococcus anginosus
Streptococcus oralis
Streptococcus mitis
Anaerobes
Prevotella intermedia
Prevotella bivia
Propionibacterium acnes
Micromonas (“Peptostreptococcus”) micros
Finegoldia (“Peptostreptococcus”) magna
Actinomyces israelii
Clostridium clostridioforme
Eubacterium lentum
Susceptibility Testing Methods
When available, the clinical microbiology laboratory should provide cumulative in vitro susceptibility test results for antimicrobial drugs used in local hospitals and practice areas to the physician as periodic reports that describe the susceptibility profile of nosocomial and community-acquired pathogens. These reports should aid the physician in selecting the most effective antimicrobial.
Dilution Techniques
Quantitative methods are used to determine antimicrobial minimum inhibitory concentra‑tions (MICs). These MICs provide estimates of the susceptibility of bacteria to antimicrobial compounds. The MICs should be determined using a standardized procedure based on dilution methods (broth, agar, or microdilution)^1,2 or equivalent using standardized inoculum and concentrations of clindamycin. The MIC values should be interpreted according to the criteria provided in Table 1.
Diffusion Techniques
Quantitative methods that require the measurement of zone diameters also pro‑vide reproducible estimates of the susceptibility of bac‑teria to antimicrobial compounds. The standardized procedure^1,3 requires the use of standardized inoculum concentrations. This procedure uses paper disks impregnated with 2 mcg of clindamycin to test the susceptibility of microorganisms to clindamycin. Reports from the laboratory providing results of the standard single-disk susceptibility test with a 2 mcg clindamycin disk should be interpreted according to the criteria in Table 1.

Table 1. Susceptibility Interpretive Criteria for Clindamycin
Pathogen | Susceptibility Interpretive Criteria
Pathogen | Minimal Inhibitory Concentrations (MIC in mcg/mL) |  |  | Disk Diffusion (Zone Diameters in mm)
Staphylococcus spp. | ≤0.5 | 1-2 | ≥4 | ≥21 | 15-20 | ≤14
Streptococcus pneumoniae and other Streptococcus spp. | ≤0.25 | 0.5 | ≥1 | ≥19 | 16-18 | ≤15
Anaerobic Bacteria | ≤2 | 4 | ≥8 | NA | NA | NA
NA=not applicable

A report of “Susceptible” indicates that the pathogen is likely to be inhibited if the antimicrobial compound in the blood reaches the concentrations usually achiev‑able. A report of “Intermediate” indicates that the result should be considered equivocal, and, if the microorgan‑ism is not fully susceptible to alternative, clinically feasi‑ble drugs, the test should be repeated. This category implies possible clinical applicability in body sites where the drug is physiologically concentrated or in situations where high dosage of drug can be used. This category also provides a buffer zone that prevents small, uncon‑trolled technical factors from causing major discrepan‑cies in interpretation.
A report of “Resistant” indicates that the pathogen is not likely to be inhibited if the antimicrobial compound in the blood reaches the con‑centrations usually achievable; other therapy should be selected.
Quality Control
Standardized susceptibility test procedures require the use of laboratory controls to monitor and ensure the accuracy and precision of the supplies and reagents used in the assay, and the techniques of the individuals performing the test.^1,2,3,4 Standard clindamycin powder should provide the MIC ranges in Table 2. For the disk diffusion technique using the 2 mcg clindamycin disk the criteria provided in Table 2 should be achieved.

Table 2. Acceptable Quality Control Ranges for Clindamycin to be Used in Validation of Susceptibility Test Results
QC Strain | Acceptable Quality Control Ranges
Minimum Inhibitory Concentration Range (mcg/mL) | Disk Diffusion (Zone Diameters in mm)
When Testing Aerobic Pathogens
Staphylococcus aureus ATCC 29213 | 0.06–0.25 | NA
Staphylococcus aureus ATCC 25923 | NA | 24–30
Streptococcus pneumoniae ATCC 49619 | 0.03–0.12 | 19–25
When Testing Anaerobes
Bacteroides fragilis ATCC 25285 | 0.5–2 | NA
Bacteroides thetaiotaomicron ATCC 29741 | 2–8 | NA
Eubacterium lentum ATCC 43055 | 0.06–0.25 | NA
NA=not applicable
ATCC® is a registered trademark of the American Type Culture Collection

INDICATIONS AND USAGE

Clindamycin hydrochloride capsules, USP are indicated in the treatment of serious infections caused by susceptible anaerobic bacteria.
Clindamycin hydrochloride capsules, USP are also indicated in the treatment of seri‑ous infections due to susceptible strains of streptococci, pneumococci, and staphylococci. Its use should be reserved for penicillin-allergic patients or other patients for whom, in the judgment of the physician, a penicillin is inappropriate. Because of the risk of colitis, as described in the WARNING box, before selecting clindamycin, the physician should consider the nature of the infection and the suitability of less toxic alternatives (e.g., erythromycin).
Anaerobes: Serious respiratory tract infections such as empyema, anaerobic pneumonitis, and lung abscess; serious skin and soft tissue infections; septicemia; intra-abdominal infections such as peritonitis and intra-abdominal abscess (typically resulting from anaerobic organisms resident in the normal gastroin‑testinal tract); infections of the female pelvis and geni‑tal tract such as endometritis, nongonococcal tubo-ovarian abscess, pelvic cellulitis, and postsurgical vaginal cuff infection.
Streptococci: Serious respiratory tract infections; seri‑ous skin and soft tissue infections.
Staphylococci: Serious respiratory tract infections; serious skin and soft tissue infections.
Pneumococci: Serious respiratory tract infections.
Bacteriologic studies should be performed to deter‑mine the causative organisms and their susceptibility to clindamycin.
To reduce the development of drug-resistant bacteria and maintain the effectiveness of clindamycin hydrochloride and other antibacterial drugs, clindamycin hydrochloride should be used only to treat or prevent infections that are proven or strongly suspected to be caused by susceptible bacte‑ria. When culture and susceptibility information are available, they should be considered in selecting or modifying antibacterial therapy. In the absence of such data, local epidemiology and susceptibility patterns may contribute to the empiric selection of therapy.

CONTRAINDICATIONS

Clindamycin hydrochloride capsules are contraindicated in individuals with a history of hypersensitivity to preparations containing clindamycin or lincomycin.

WARNINGS

See WARNING box.
Clostridium difficile associated diarrhea (CDAD) has been reported with use of nearly all antibacterial agents, including clindamycin hydrochloride, and may range in severity from mild diarrhea to fatal colitis. Treatment with antibacterial agents alters the normal flora of the colon, leading to overgrowth of C. difficile.
C. difficile produces toxins A and B, which contribute to the development of CDAD. Hypertoxin producing strains of C. difficile cause increased morbidity and mortality, as these infections can be refractory to antimicrobial therapy and may require colectomy. CDAD must be considered in all patients who present with diarrhea following antibiotic use. Careful medical history is necessary since CDAD has been reported to occur over two months after the administration of antibacterial agents.
If CDAD is suspected or confirmed, ongoing antibiotic use not directed against C. difficile may need to be discontinued. Appropriate fluid and electrolyte management, protein supplementation, antibiotic treatment of C. difficile, and surgical evaluation should be instituted as clinically indicated.
A careful inquiry should be made concerning previous sensitivities to drugs and other allergens.
Usage in Meningitis
Since clindamycin does not dif‑fuse adequately into the cerebrospinal fluid, the drug should not be used in the treatment of meningitis.

PRECAUTIONS

General

Review of experience to date suggests that a sub‑group of older patients with associated severe illness may tolerate diarrhea less well. When clindamycin is indicated in these patients, they should be carefully monitored for change in bowel frequency.
Clindamycin hydrochloride should be prescribed with caution in individuals with a history of gastrointestinal disease, particularly colitis.
Clindamycin hydrochloride should be prescribed with caution in atopic individuals.
Indicated surgical procedures should be performed in conjunction with antibiotic therapy.
The use of clindamycin hydrochloride occasionally results in over‑growth of nonsusceptible organisms—particularly yeasts. Should superinfections occur, appropriate measures should be taken as indicated by the clinical situation.
Clindamycin dosage modification may not be neces‑sary in patients with renal disease. In patients with mod‑erate to severe liver disease, prolongation of clindamycin half-life has been found. However, it was postulated from studies that when given every eight hours, accumulation should rarely occur. Therefore, dosage modification in patients with liver disease may not be necessary. However, periodic liver enzyme deter‑minations should be made when treating patients with severe liver disease.
Prescribing clindamycin hydrochloride in the absence of a proven or strongly suspected bacterial infection or a prophylac‑tic indication is unlikely to provide benefit to the patient and increases the risk of the development of drug-resis‑tant bacteria.

Information for Patients

Patients should be counseled that antibacterial drugs, including clindamycin hydrochloride, should only be used to treat bacterial infections. They do not treat viral infections (e.g., the common cold). When clindamycin hydrochloride is pre‑scribed to treat a bacterial infection, patients should be told that although it is common to feel better early in the course of therapy, the medication should be taken exactly as directed. Skipping doses or not completing the full course of therapy may (1) decrease the effec‑tiveness of the immediate treatment and (2) increase the likelihood that bacteria will develop resistance and will not be treatable by clindamycin hydrochloride or other antibacte‑rial drugs in the future.
Diarrhea is a common problem caused by antibiotics which usually ends when the antibiotic is discontinued. Sometimes after starting treatment with antibiotics, patients can develop watery and bloody stools (with or without stomach cramps and fever) even as late as two or more months after having taken the last dose of the antibiotic. If this occurs, patients should contact their physician as soon as possible.

Laboratory Tests

During prolonged therapy, periodic liver and kidney function tests and blood counts should be performed.

Drug Interactions

Clindamycin has been shown to have neuromuscular blocking properties that may enhance the action of other neuromuscular blocking agents. Therefore, it should be used with caution in patients receiving such agents.
Antagonism has been demonstrated between clindamycin and erythromycin in vitro. Because of possible clinical significance, these two drugs should not be administered concurrently.

Carcinogenesis, Mutagenesis, Impairment of Fertility

Long-term studies in animals have not been per‑formed with clindamycin to evaluate carcinogenic poten‑tial. Genotoxicity tests performed included a rat micronucleus test and an Ames Salmonella reversion test. Both tests were negative.
Fertility studies in rats treated orally with up to 300 mg/kg/day (approximately 1.6 times the highest rec‑ommended adult human dose based on mg/m^2) revealed no effects on fertility or mating ability.

Pregnancy

Teratogenic Effects

Pregnancy Category B
Reproduction studies performed in rats and mice using oral doses of clindamycin up to 600 mg/kg/day (3.2 and 1.6 times the highest recommended adult human dose based on mg/m^2, respectively) or subcuta‑neous doses of clindamycin up to 250 mg/kg/day (1.3 and 0.7 times the highest recommended adult human dose based on mg/m^2, respectively) revealed no evi‑dence of teratogenicity.
There are, however, no adequate and well-controlled studies in pregnant women. Because animal reproduc‑tion studies are not always predictive of the human response, this drug should be used during pregnancy only if clearly needed.

Nursing Mothers

Clindamycin has been reported to appear in breast milk in the range of 0.7 to 3.8 mcg/mL.

Pediatric Use

When clindamycin hydrochloride is administered to the pediatric population (birth to 16 years), appropriate monitoring of organ system functions is desirable.

Geriatric Use

Clinical studies of clindamycin did not include suffi‑cient numbers of patients age 65 and over to determine whether they respond differently from younger patients. However, other reported clinical experience indicates that antibiotic-associated colitis and diarrhea (due to Clostridium difficile) seen in association with most anti‑biotics occur more frequently in the elderly (>60 years) and may be more severe. These patients should be carefully monitored for the development of diarrhea.
Pharmacokinetic studies with clindamycin have shown no clinically important differences between young and elderly subjects with normal hepatic function and normal (age-adjusted) renal function after oral or intravenous administration.

ADVERSE REACTIONS

The following reactions have been reported with the use of clindamycin.
Gastrointestinal: Abdominal pain, pseudomembranous colitis, esophagitis, nausea, vomiting, and diarrhea (see WARNING box). The onset of pseudomembranous coli‑tis symptoms may occur during or after antibacterial treatment (see WARNINGS).
Hypersensitivity Reactions: Generalized mild to moder‑ate morbilliform-like (maculopapular) skin rashes are the most frequently reported adverse reactions.
Vesiculobullous rashes, as well as urticaria, have been observed during drug therapy. Rare instances of erythema multiforme, some resembling Stevens-Johnson syndrome, and a few cases of anaphylactoid reactions have also been reported.
Skin and Mucous Membranes: Pruritus, vaginitis, and rare instances of exfoliative dermatitis have been reported. (See Hypersensitivity Reactions.)
Liver: Jaundice and abnormalities in liver function tests have been observed during clindamycin therapy.
Renal: Although no direct relationship of clindamycin to renal damage has been established, renal dysfunc‑tion as evidenced by azotemia, oliguria, and/or proteinuria has been observed in rare instances.
Hematopoietic: Transient neutropenia (leukopenia) and eosinophilia have been reported. Reports of agranulocytosis and thrombocytopenia have been made. No direct etiologic relationship to concurrent clindamycin therapy could be made in any of the foregoing.
Musculoskeletal: Rare instances of polyarthritis have been reported.

OVERDOSAGE

Significant mortality was observed in mice at an intra‑venous dose of 855 mg/kg and in rats at an oral or sub‑cutaneous dose of approximately 2618 mg/kg. In the mice, convulsions and depression were observed.
Hemodialysis and peritoneal dialysis are not effective in removing clindamycin from the serum.

DOSAGE AND ADMINISTRATION

If significant diarrhea occurs during therapy, this antibiotic should be discontinued (see WARNING box).
Adults
Serious infections—150 to 300 mg every 6 hours. More severe infections—300 to 450 mg every 6 hours.
Pediatric Patients
Serious infections—8 to 16 mg/kg/day (4 to 8 mg/lb/day) divided into three or four equal doses. More severe infections—16 to 20 mg/kg/day (8 to 10 mg/lb/day) divided into three or four equal doses.
To avoid the possibility of esophageal irritation, clindamycin hydrochloride capsules should be taken with a full glass of water.
Serious infections due to anaerobic bacteria are usu‑ally treated with clindamycin injection. However, in clinically appropriate circum‑stances, the physician may elect to initiate treatment or continue treatment with clindamycin hydrochloride capsules.
In cases of β-hemolytic streptococcal infections, treat‑ment should continue for at least 10 days.

HOW SUPPLIED

Clindamycin Hydrochloride Capsules USP, 300 mg are light blue opaque/light blue opaque size ‘0’ hard gelatin capsule filled with white to off-white powder and imprinted with ‘C’ on light blue opaque cap and ‘40’ on light blue opaque body with black ink.

Bottles of 20 NDC 63187-127-20

Bottles of 21 NDC 63187-127-21

Bottles of 28 NDC 63187-127-28

Bottles of 30 NDC 63187-127-30

Bottles of 40 NDC 63187-127-40

Bottles of 60 NDC 63187-127-60

ANIMAL TOXICOLOGY

One-year oral toxicity studies in Spartan Sprague-Dawley rats and beagle dogs at dose levels up to 300 mg/kg/day (approximately 1.6 and 5.4 times the highest recommended adult human dose based on mg/m^2, respectively) have shown clindamycin to be well toler‑ated. No appreciable difference in pathological findings has been observed between groups of animals treated with clindamycin and comparable control groups. Rats receiving clindamycin hydrochloride at 600 mg/kg/day (approximately 3.2 times the highest recommended adult human dose based on mg/m^2) for 6 months toler‑ated the drug well; however, dogs dosed at this level (approximately 10.8 times the highest recommended adult human dose based on mg/m^2) vomited, would not eat, and lost weight.

REFERENCES

- CLSI. Performance Standards for Antimicrobial Susceptibility Testing: Twentieth Informational Supplement. CLSI document M 100-S20. Wayne, PA: Clinical and Laboratory Standards Institute; 2010.
- CLSI. Methods for Dilution Antimicrobial Susceptibility Tests for Bacteria that Grow Aerobically; Approved Standard – Eighth Edition. CLSI document M07-A8. Wayne, PA: Clinical and Laboratory Standards Institute; 2009.
- CLSI. Performance Standards for Antimicrobial Disk Susceptibility Tests; Approved Standard - Tenth Edition. CLSI document M02-A10. Wayne, PA: Clinical and Laboratory Standards Institute; 2009.
- CLSI. Methods for Antimicrobial Susceptibility Testing of Anaerobic Bacteria; Approved Standard-Seventh Edition. CLSI document M11-A7. Wayne, PA: Clinical and Laboratory Standards Institute; 2007.

Manufactured for:
Aurobindo Pharma USA, Inc.
2400 Route 130 North
Dayton, NJ 08810
Manufactured by:
Aurobindo Pharma Limited
Hyderabad–500 072, India
Revised: 01/2012

Repackaged by:
Proficient Rx LP
Thousand Oaks, CA 91320